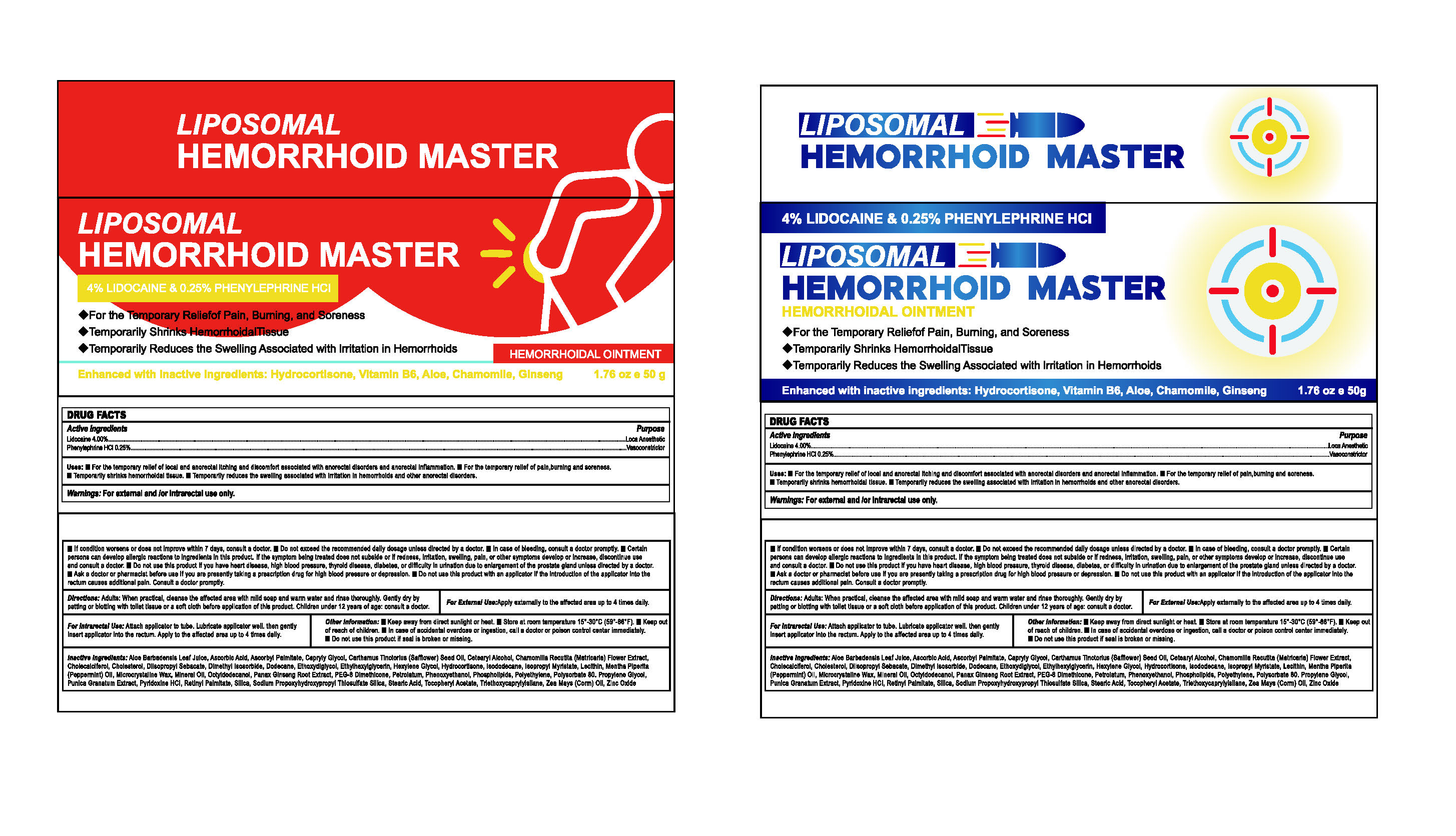 DRUG LABEL: LIPOSOMAL HEMORRHOID MASTER
NDC: 84735-008 | Form: OINTMENT
Manufacturer: Hengyang Chuangjiujia Trading Co., Ltd.
Category: otc | Type: HUMAN OTC DRUG LABEL
Date: 20250512

ACTIVE INGREDIENTS: LIDOCAINE 4 g/100 g; PHENYLEPHRINE 0.25 g/100 g
INACTIVE INGREDIENTS: PROPYLENE GLYCOL; SODIUM HYALURONATE; PYRIDOXINE HCL; CHAMOMILE; PHENOXYETHANOL; WATER; GLYCERIN; ASCORBIC ACID; TRIETHANOLAMINE; ALOE BARBADENSIS LEAF; MINERAL OIL; TOCOPHEROL; DEXPANTHENOL; ALLANTOIN; ETHYLHEXYLGLYCERIN; CARBOMER; PETROLATUM; ASIAN GINSENG; POLYSORBATE 80

84735-008 LIPOSOMAL HEMORRHOID MASTER

ACTIVE INGREDIENT

Lidocaine HCl 4%

Phenylephrine HCl 0.25%

PURPOSE

Loca Anesthetic
Vasoconstrictor

INDICATIONS AND USAGE

Uses. Forthe temporany relief of local and anorectal iching and discomfot asociated with anoreclal isorders and anorectalimammation.
Forthe temporany reief of pain,buring and sorenes.
Temporarily shrinks hemorthoidal tisue, Temporarily reduces the sweling associated with iritation in hemorthoids and other anorectal disorders.

WARNINGS

For external and /or intrarectal use only.

Do not use this product if you have heart disease, high blood pressure, thyroid disease, diabetes, or difficulty in urination due to enlargement of the prostate gland unless directed by a doctor.
Ask a doctor or pharmacist before use if you are presently taking a prescription drug for high blood pressure or depression.
Do not use this product with an applicator if the introduction of the applicator into the rectum causes additional pain. Consult a doctor promptly.

WHEN USING

If condition worsens or does not improve within 7 days, consult a doctor.
Do not exceed the recommended daily dosage unless directed by a doctor.
In case of bleeding, consult a doctor promptly.

STOP USE

Certain persons can develop allergic reactions to ingredients in this product. If the symptom being treated does not subside or if redness, irritation, swelling, pain, or other symptoms develop or increase, discontinue use and consult a doctor.

Keep away from direct sunlight or heat.

DOSAGE AND ADMINISTRATION

Directions: Adults: When practical, cleanse the affected area with mild soap and warm water and rinse thoroughly. Gently dry by patting or blotting with toilet tissue or a soft cloth before application of this product. Children under 12 years of age: consult a doctor.

INACTIVE INGREDIENT

Petrolatum
Aloe Barbadensis Leaf Extract
Glycerin
Mineral Oil
Chamomilla Recutita (Matricaria) Flower Extract
Tocopherol
Ascorbic Acid
Pyridoxine HCl
Ginseng Extract
Propylene Glycol
Sodium Hyaluronate
Polysorbate 80
Panthenol
Allantoin
Phenoxyethanol
Ethylhexylglycerin
Carbomer
Triethanolamine
Water